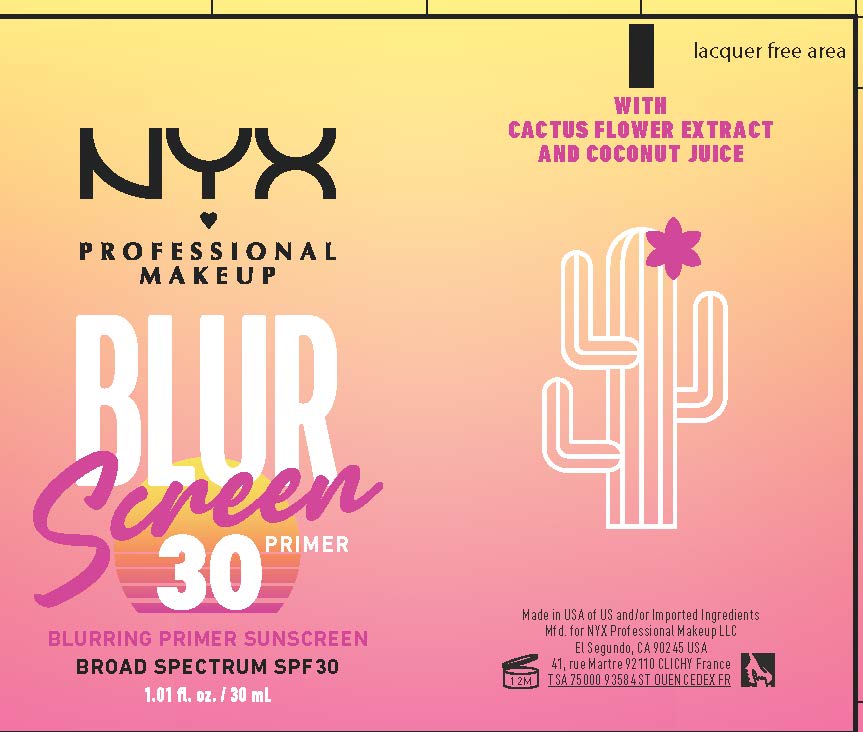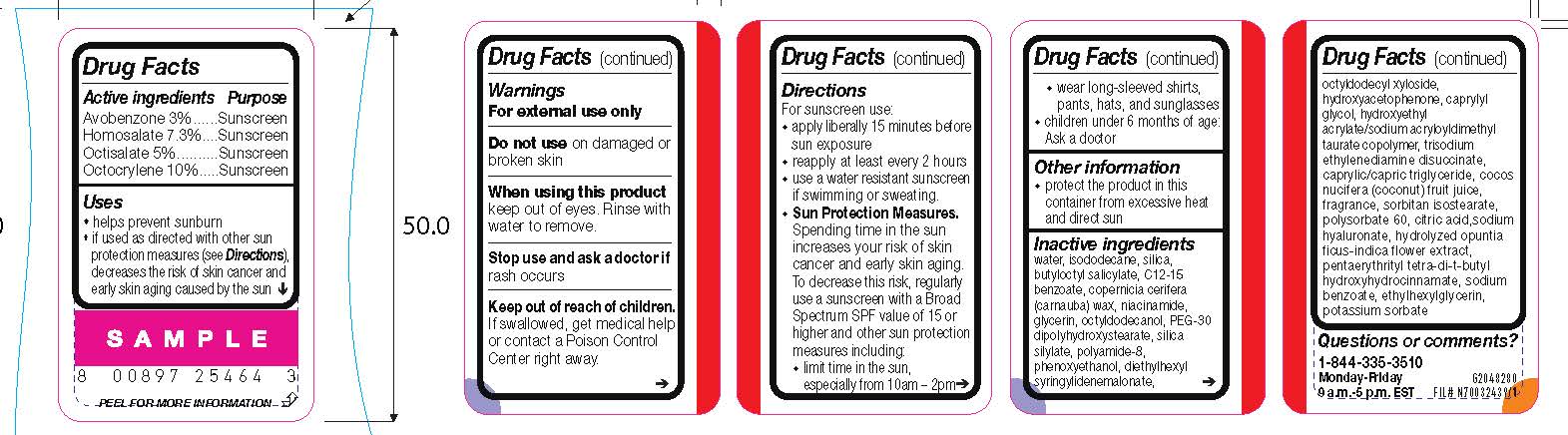 DRUG LABEL: NYX Professional Makeup Blurscreen Primer Broad Spectrum SPF 30 Sunscreen
NDC: 49967-990 | Form: LOTION
Manufacturer: L'Oreal USA Products Inc
Category: otc | Type: HUMAN OTC DRUG LABEL
Date: 20240716

ACTIVE INGREDIENTS: AVOBENZONE 30 mg/1 mL; HOMOSALATE 73 mg/1 mL; OCTISALATE 50 mg/1 mL; OCTOCRYLENE 100 mg/1 mL
INACTIVE INGREDIENTS: WATER; ISODODECANE; SILICON DIOXIDE; BUTYLOCTYL SALICYLATE; ALKYL (C12-15) BENZOATE; CARNAUBA WAX; NIACINAMIDE; GLYCERIN; OCTYLDODECANOL; PEG-30 DIPOLYHYDROXYSTEARATE; POLYAMIDE-8 (4500 MW); PHENOXYETHANOL; DIETHYLHEXYL SYRINGYLIDENEMALONATE; OCTYLDODECYL XYLOSIDE; HYDROXYACETOPHENONE; CAPRYLYL GLYCOL; HYDROXYETHYL ACRYLATE/SODIUM ACRYLOYLDIMETHYL TAURATE COPOLYMER (100000 MPA.S AT 1.5%); TRISODIUM ETHYLENEDIAMINE DISUCCINATE; MEDIUM-CHAIN TRIGLYCERIDES; COCONUT JUICE; SORBITAN ISOSTEARATE; POLYSORBATE 60; CITRIC ACID MONOHYDRATE; HYALURONATE SODIUM; PENTAERYTHRITOL TETRAKIS(3-(3,5-DI-TERT-BUTYL-4-HYDROXYPHENYL)PROPIONATE); SODIUM BENZOATE; ETHYLHEXYLGLYCERIN; POTASSIUM SORBATE

Drug Facts

Active ingredients

Avobenzone 3%

Homosalate 7.3%

Octisalate 5%

Octocrylene 10%

Purpose

Sunscreen

Uses

- helps prevent sunburn
- if used as directed with other sun protection measures (see Directions), decreases the risk of skin cancer and early skin aging caused by the sun

Warnings

For external use only

Do not use

on damaged or broken skin

When using this product

keep out of eyes. Rinse with water to remove.

Stop use and ask a doctor if

rash occurs

Keep out of reach of children.

If swallowed, get medical help or contact a Poison Control Center right away.

Directions

For sunscreen use:

● apply liberally 15 minutes before sun exposure

● reapply at least every 2 hours

● use a water resistant sunscreen if swimming or sweating

● Sun Protection Measures. Spending time in the sun increases your risk of skin cancer and early skin aging. To decrease this risk, regularly use a sunscreen with a Broad Spectrum SPF value of 15 or higher and other sun protection measures including:

● limit time in the sun, especially from 10 a.m. – 2 p.m.

● wear long-sleeved shirts, pants, hats, and sunglasses

● children under 6 months of age: Ask a doctor

Other information

protect the product in this container from excessive heat and direct sun

Inactive ingredients

water, isododecane, silica, butyloctyl salicylate, c12-15 alkyl benzoate, copernicia cerifera (carnauba) wax, niacinamide, glycerin, octyldodecanol, PEG-30 dipolyhydroxystearate, silica silylate, polyamide-8, phenoxyethanol, diethylhexyl syringylidenemalonate, octyldodecyl xyloside, hydroxyacetophenone, caprylyl glycol, hydroxyethyl acrylate/sodium acryloyldimethyl taurate copolymer, trisodium ethylenediamine disuccinate, caprylic/capric triglyceride, cocos nucifera (coconut) fruit juice, fragrance, sorbitan isostearate, polysorbate 60, citric acid, sodium hyaluronate, hydrolyzed opuntia ficus-indica flower extract, pentaerythrityl tetra-di-t-butyl hydroxyhydrocinnamate, sodium benzoate, ethylhexylglycerin, potassium sorbate